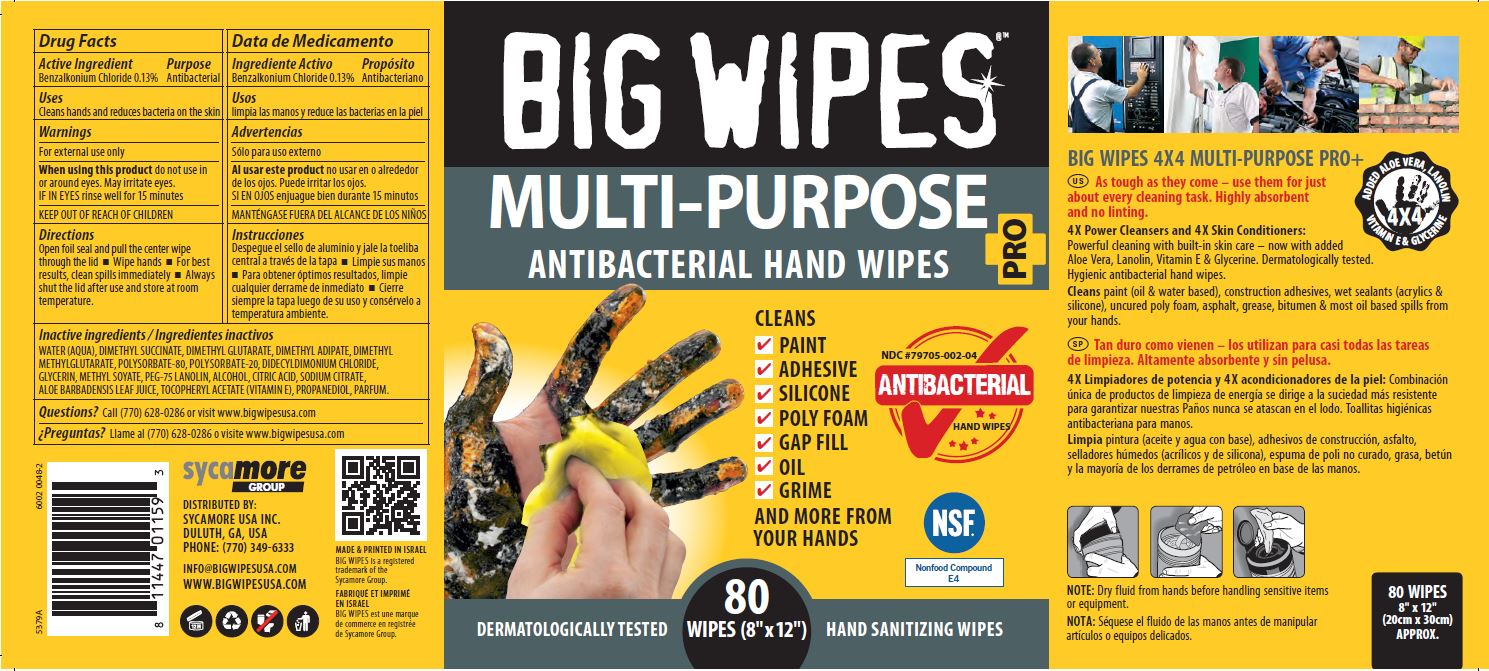 DRUG LABEL: BIG WIPES Multi-Purpose
NDC: 79705-002 | Form: CLOTH
Manufacturer: Sycamore USA Inc.
Category: otc | Type: HUMAN OTC DRUG LABEL
Date: 20221123

ACTIVE INGREDIENTS: BENZALKONIUM CHLORIDE 1.3 mg/1 mL
INACTIVE INGREDIENTS: METHYL SOYATE; DIMETHYL GLUTARATE; DIMETHYL METHYLGLUTARATE; WATER; DIMETHYL SUCCINATE; DIMETHYL ADIPATE; POLYSORBATE 20; PROPANEDIOL; ALOE VERA LEAF; SODIUM CITRATE; DIDECYLDIMONIUM CHLORIDE; PEG-75 LANOLIN; CITRIC ACID MONOHYDRATE; .ALPHA.-TOCOPHEROL ACETATE; POLYSORBATE 80; GLYCERIN; ALCOHOL

BIG WIPES
MULTI-PURPOSE

Active Ingredient

Benzalkonium Chloride 0.13%

Purpose

Antibacterial

Uses

Ceans hands and reduces bacteria on the skin

Warnings

For external use only

When using this product do not use in or around eyes. May irritate eyes.

If IN EYES rinse well for 15 minutes

Directions

Open foil seal and pull the center wipe through the lid

- Wipe hands
- For best results, clean spills immediately
- Always shut the lid after use and store at room temperature.

Inactive ingredients

WATER (AQUA), DIMETHYL SUCCINATE, DIMETHYL GUTARATE, DIMETHYL ADIPATE, DIMETHYL METHYLGLUTARATE. POLYSORBATE-80, POLYSORBATE-20, DIDECYLDIMONIUM CHLORIDE, GLYCERIN, METHYL SOYATE, PEG-75 LANOLIN, ALCOHOL, CITRIC ACID, SODIUM CITRATE, ALOE BARBADENSIS LEAF JUICE, TOCOPHERYL ACETATE (VITAMIN E), PROPANEDIOL, PARFUM.

Questions?

Call (770) 628-0286 or visit www.bigwipesusa.com

PACKAGE LABEL

BIG WIPES

MULTI-PURPOSE

ANTIBACTERIAL HAND WIPES

PRO+

CLEANS

PAINT

ADHESIVE

SILICONE

POLY FOAM

GAP FILL

OIL

GRIME

and MORE FROM

YOUR HANDS

4x4 FORMULA

TOUGH ON

GRIME

KIND TO YOUR HANDS

NDC # 79705-002-04

ANTIBACTERIAL

check mark

Hand Wipes

NSF

Nonfood Compound

E4

DERMATOLOGICALLY TESTED

80

WIPES (8" x 12")

HAND SANITIZER WIPES